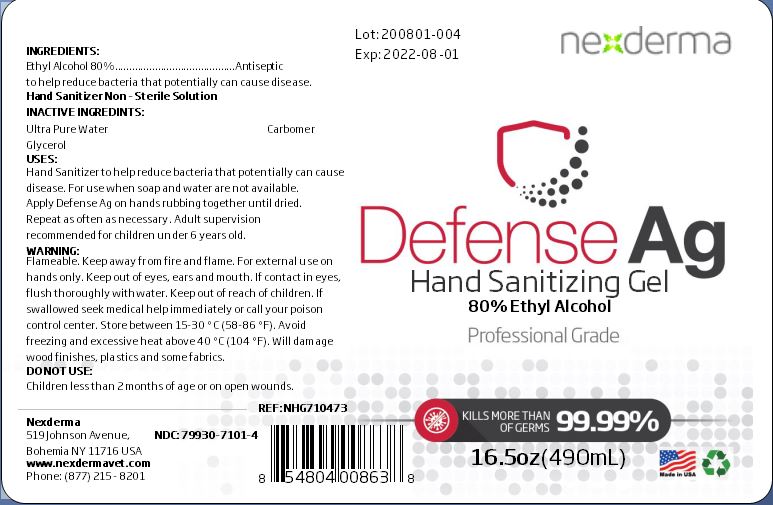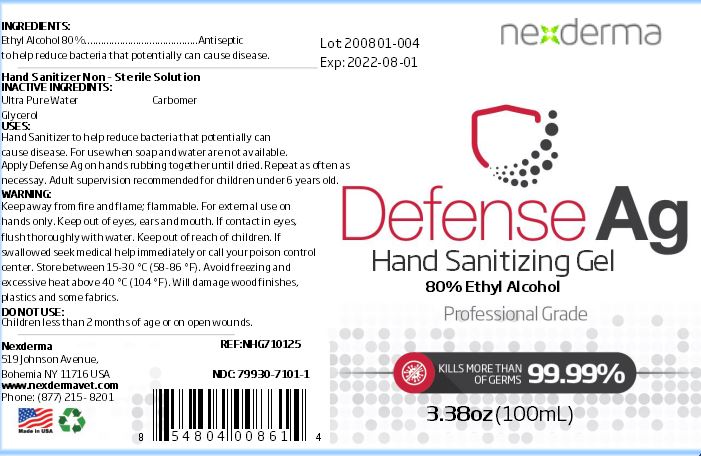 DRUG LABEL: Defense Ag
NDC: 79930-7101 | Form: GEL
Manufacturer: Nederma Inc
Category: otc | Type: HUMAN OTC DRUG LABEL
Date: 20200721

ACTIVE INGREDIENTS: ALCOHOL 80 mL/100 mL
INACTIVE INGREDIENTS: CARBOMER 940 0.25 mL/100 mL; WATER 10 mL/100 mL; GLYCERIN 1 mL/100 mL

Active Ingredient

Ethyl Alcohol 80% - Antiseptic to help reduce bacteria that potentialy can cause disease.

Inactive Ingredients

Glycerol

Carbomer

Ultra Pure Water

Uses

Hand Sanitizer to help reduce bacteria that potentially can cause disease. For use when soap and water are not available. Apply Defense Ag on hands rubbing together until dried. Repeat as often as necessary.

KEEP OUT OF REACH OF CHILDREN

Adult super vision recommended for children under 6 years old.

WARNINGS

Keep away from fire and flame.

Flammable.

For external use on hands only.

Keep out of eyes, ears and mouth.

If contact in eyes, flush thoroughly with water.

Keep out of reach of children.

If swallowed seek medical help immediately or call your poison control center.

Store between 15-30C (58-86F).

Avoid freezing and excessive heat above 40C(104F).

will damage wood finishes, plastics and some fabrics.

DO NOT USE

Children less than 2 months of age or on open wounds.

Dosage: upto 10 times a day

Place enough product on hands to cover all surfaces. Rub hands together until dry.

Administration: Topical

PURPOSE

Purpose: To help reduce bacteria that potentially can cause disease. For use when soap and water are not available.